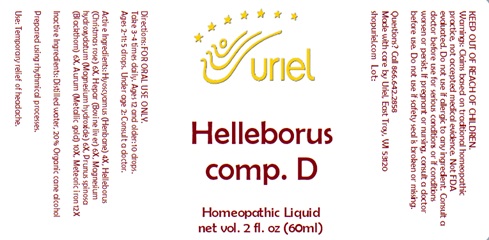 DRUG LABEL: Helleborus comp. D
NDC: 48951-5118 | Form: LIQUID
Manufacturer: Uriel Pharmacy Inc.
Category: homeopathic | Type: HUMAN OTC DRUG LABEL
Date: 20241217

ACTIVE INGREDIENTS: GOLD 10 [hp_X]/1 mL; IRON 12 [hp_X]/1 mL; HYOSCYAMUS NIGER LEAF 4 [hp_X]/1 mL; HELLEBORUS NIGER ROOT 6 [hp_X]/1 mL; MAGNESIUM CATION 6 [hp_X]/1 mL; BEEF LIVER 6 [hp_X]/1 mL; SLOE 6 [hp_X]/1 mL
INACTIVE INGREDIENTS: ALCOHOL; WATER

Helleborus comp. D

INDICATIONS AND USAGE

Directions: FOR ORAL USE ONLY.

DOSAGE AND ADMINISTRATION

Take 3-4 times daily. Ages 12 and older: 10 drops. Ages 2-11: 5 drops. Under age 2: Consult a doctor.

ACTIVE INGREDIENT

Active Ingredients: Hyoscyamus (Henbane) 4X, Helleborus (Christmas rose) 6X, Hepar (Bovine liver) 6X, Magnesium hydroxydatum (Magnesium hydroxide) 6X, Prunus spinosa (Blackthorn) 6X, Aurum (Metallic gold) 10X, Meteoric iron 12X

Inactive Ingredients: Distilled water, 20% Organic cane alcohol

Prepared using rhythmical processes.

PURPOSE

Use: Temporary relief of headache.

KEEP OUT OF REACH OF CHILDREN.

WARNINGS

Warnings: Claims based on traditional homeopathic practice, not accepted medical evidence. Not FDA evaluated. Do not use if allergic to any ingredient. Consult a doctor before use for serious conditions or if conditions worsen or persist. If pregnant or nursing, consult a doctor before use. Do not use if safety seal is broken or missing.

Questions? Call 866.642.2858
Made with care by Uriel, East Troy, WI 53120
shopuriel.com Lot: